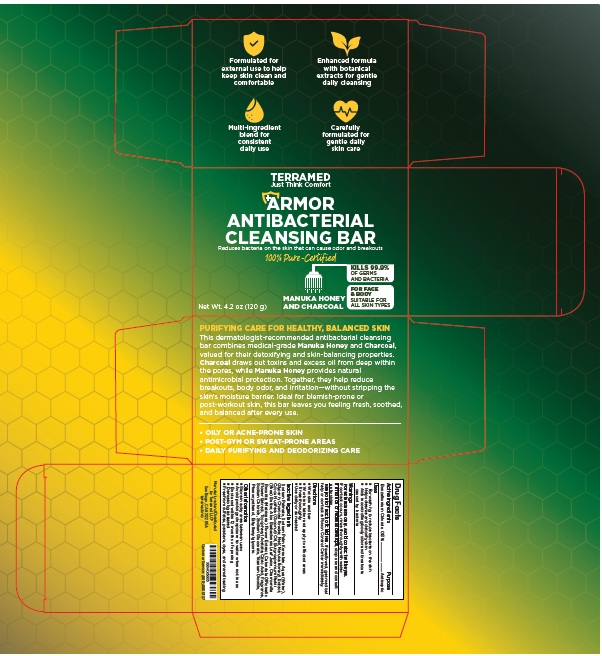 DRUG LABEL: Terramed Just Think Comfort Armor Antibacterial Cleansing Bar
NDC: 83004-033 | Form: SOAP
Manufacturer: Rida LLC
Category: otc | Type: HUMAN OTC DRUG LABEL
Date: 20260204

ACTIVE INGREDIENTS: BENZALKONIUM CHLORIDE 0.13 g/100 g
INACTIVE INGREDIENTS: SODIUM PALMATE; SODIUM PALM KERNELATE; WATER; GLYCERIN; CHARCOAL POWDER; HONEY; COCOS NUCIFERA (COCONUT) OIL; BUTYROSPERMUM PARKII (SHEA) BUTTER; ALOE BARBADENSIS LEAF JUICE; CHAMOMILE; CALENDULA OFFICINALIS FLOWER; .ALPHA.-TOCOPHEROL ACETATE; CITRIC ACID MONOHYDRATE; FRAGRANCE 13576; SODIUM CHLORIDE; SODIUM GLUCONATE; TITANIUM DIOXIDE; PHENOXYETHANOL; ETHYLHEXYLGLYCERIN

Active ingredient

Benzalkonium Chloride (0.13%)

Purpose

Antiseptic

Uses

- For washing to reduce bacteria on the skin
- Helps cleanse and detoxify skin
- Aids in controlling body odor and breakouts caused by bacteria

Warnings

For external use only. Avoid contact with the eyes. If contact occurs, rinse thoroughly with water.

If irritation or redness develops, stop use and consult a physician.

Keep out of reach of children. If swallowed, get medical help or contact a Poison Control Center immediately.

Directions

- Wet skin and bar
- Work into lather and apply to affected areas
- Rinse thoroughly
- Use daily or as needed

Inactive ingredients

Sodium Palmate, Sodium Palm Kernelate, Aqua (Water), Glycerin, Charcoal Powder, Mel (Manuka Honey) Extract, Cocos Nucifera (Coconut) Oil, Butyrospermum Parkii (Shea) Butter, Aloe Barbadensis Leaf Juice, Chamomilla Recutita (Matricaria) Flower Extract, Calendula Officinalis Flower Extract, Tocopheryl Acetate, Citric Acid, Fragrance, Sodium Chloride, Sodium Gluconate, Titanium Dioxide, Phenoxyethanol, Ethylhexylglycerin.

Other Information

- Store in a dry area between uses
- Avoid prolonged exposure to water when not in use
- Best used within 12 months of opening
- Dermatologist tested
- Free from sulfates, parabens, dyes, and animal testing